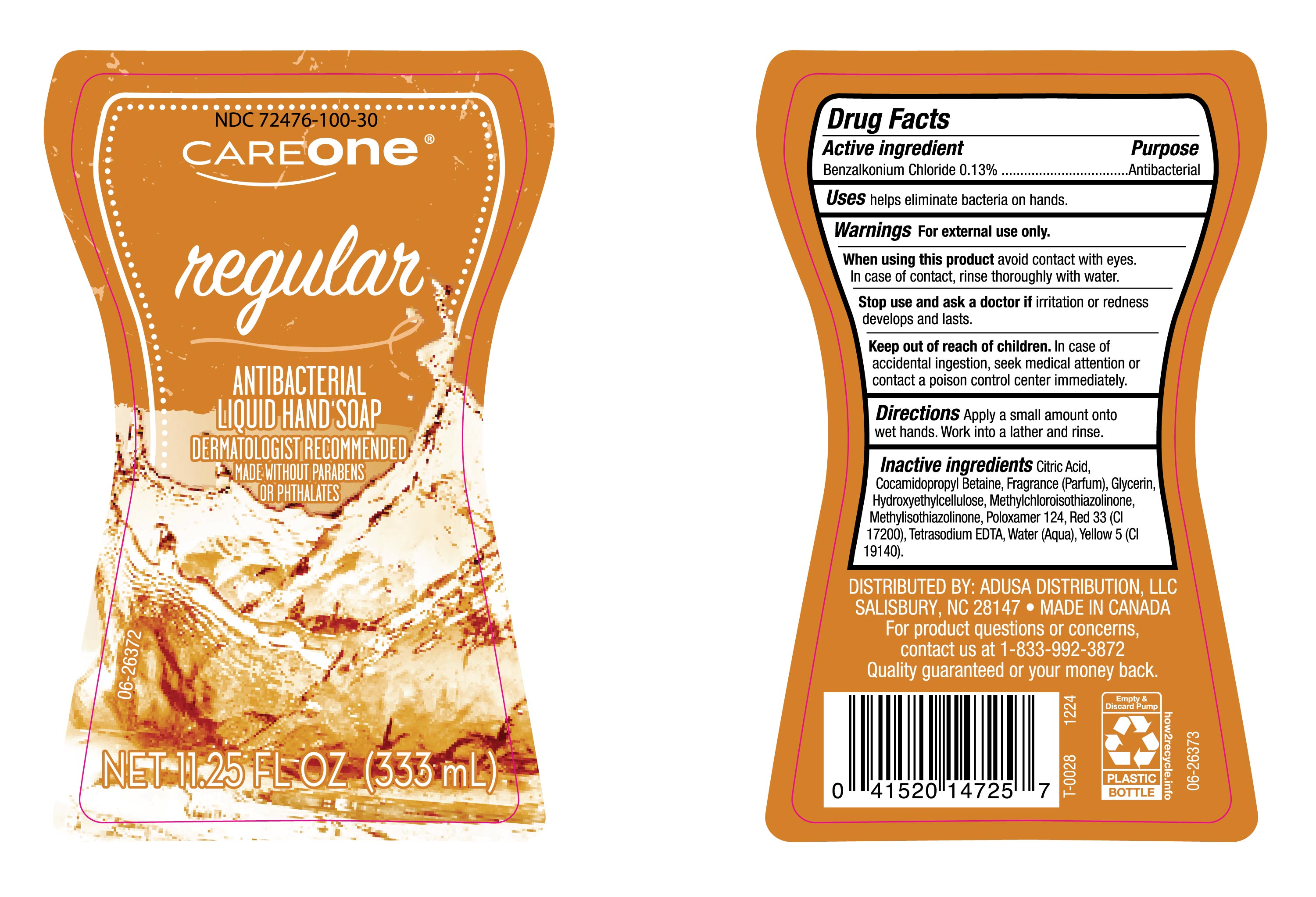 DRUG LABEL: Care One Regular
NDC: 72476-100 | Form: LIQUID
Manufacturer: RETAIL BUSINESS SERVICES , LLC
Category: otc | Type: HUMAN OTC DRUG LABEL
Date: 20250119

ACTIVE INGREDIENTS: BENZALKONIUM CHLORIDE 130 mg/100 mL
INACTIVE INGREDIENTS: FRAGRANCE CLEAN ORC0600327; CITRIC ACID; COCAMIDOPROPYL BETAINE; METHYLCHLOROISOTHIAZOLINONE; YELLOW 5; WATER; GLYCERIN; METHYLISOTHIAZOLINONE; POLOXAMER 124; RED 33; TETRASODIUM EDTA; HYDROXYETHYLCELLULOSE

NDC-72476-100, Careone regular Anibacterial Liquid Hand Soap.

Active Ingredient

Benzalkonium Chloride 0.13%

Purpose

Antibacterial

Usage

Helps eliminate bacteria on hands

Warnings

For external use only.

When using this product

avoid contact with eyes. In case of contact, rinse thoroughly with water.

Stop use and ask a doctor if

irritation or redness develops and lasts.

Keep out of reach of children.

In case of accidental ingestion, seek medical attention or contact a poison control center immediately.

Direction

Apply a small amount onto wet hands.Work into a lather and rise.

Inactive Ingredients

Citric Acid, Cocamidopropyl Betaine, Fragrace (Parfum), Glycerin, Hydroxyethylcellulose, Methylchloroisothiazolinone, Methylisothiazolinone, Poloxamer 124, Red 33 (CI 17200), Tetrasodium EDTA, Water (Aqua), Yellow 5 (CI 19140).